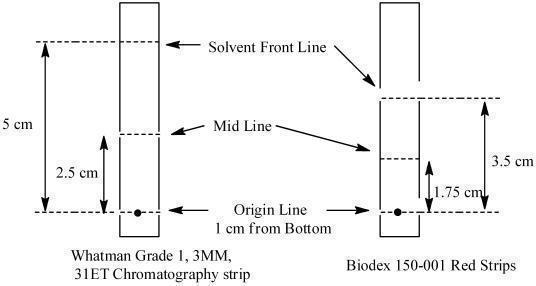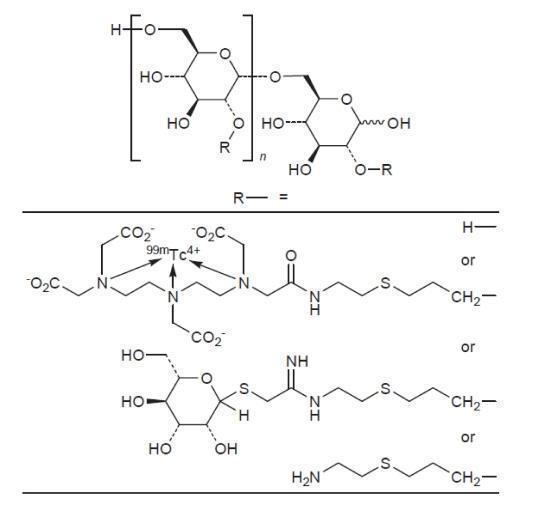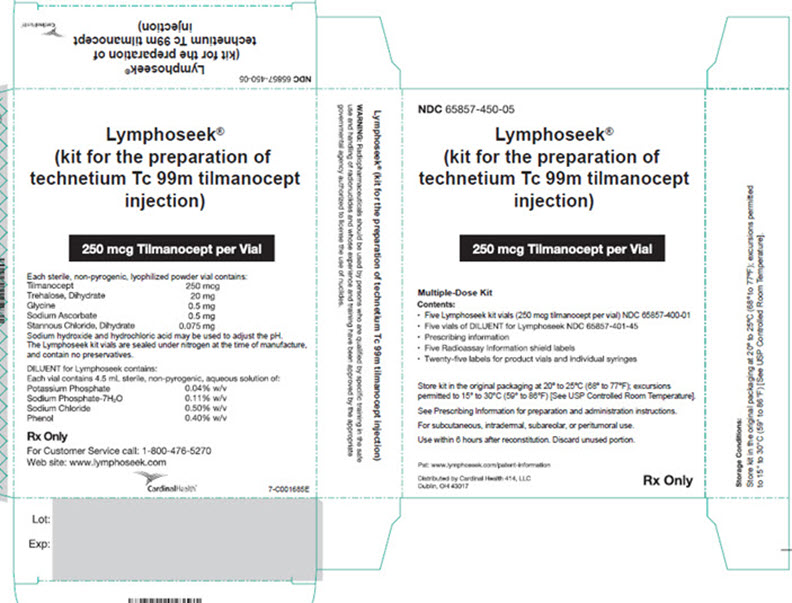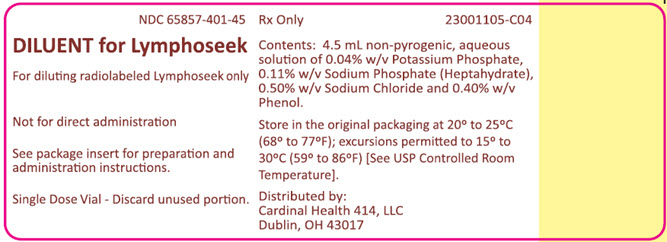 DRUG LABEL: Kit for the preparation of Lymphoseek (technetium Tc 99m tilmanocept)
NDC: 65857-425 | Form: KIT | Route: INTRADERMAL
Manufacturer: Cardinal Health 414, LLC
Category: prescription | Type: HUMAN PRESCRIPTION DRUG LABEL
Date: 20250908

ACTIVE INGREDIENTS: TECHNETIUM TC-99M TILMANOCEPT 250 ug/1 1
INACTIVE INGREDIENTS: TREHALOSE DIHYDRATE 20 mg/1 1; GLYCINE 0.5 mg/1 1; SODIUM ASCORBATE 0.5 mg/1 1; STANNOUS CHLORIDE 0.075 mg/1 1; SODIUM HYDROXIDE; HYDROCHLORIC ACID; NITROGEN

HIGHLIGHTS OF PRESCRIBING INFORMATION

These highlights do not include all the information needed to use LYMPHOSEEK safely and effectively. See full prescribing information for LYMPHOSEEK.
Lymphoseek (kit for the preparation of technetium Tc 99m tilmanocept injection) for, subcutaneous, intradermal, subareolar, or peritumoral use
Initial U.S. Approval: 2013

1 INDICATIONS AND USAGE

Lymphoseek is a radioactive diagnostic agent indicated with or without scintigraphic imaging for:

- Lymphatic mapping using a handheld gamma counter to locate lymph nodes draining a primary tumor site in adult and pediatric patients age one month and older with solid tumors for which this procedure is a component of intraoperative management. (1)
- Guiding sentinel lymph node biopsy using a handheld gamma counter in patients with clinically node negative squamous cell carcinoma of the oral cavity, breast cancer or melanoma. (1)

2 DOSAGE AND ADMINISTRATION

- Lymphoseek is supplied as a kit and must be prepared by radiolabeling with technetium Tc 99m and diluting with the supplied diluent or pharmacy-available sterile 0.9% sodium chloride injection prior to use. (2.3)
- Use aseptic technique and radiation safety precautions during Lymphoseek preparation and handling. Determine the total injection volume and number of sites to be injected for each patient before preparing Lymphoseek. (2.1, 2.3)
- Recommended dose of Lymphoseek is 18.5 MBq (0.5 mCi) administered at least 15 minutes before initiating intraoperative lymphatic mapping or sentinel node biopsy procedures: complete these procedures within 15 hours of Lymphoseek injection. (2.2, 2.3)
- Recommended routes of administration are intradermal, subcutaneous, subareolar, or peritumoral. (2.3)
- Use radiolabeled Lymphoseek within 6 hours of its preparation. (2.3)
- See Full Prescribing Information for important preparation and administration instructions. (2)

3 DOSAGE FORMS AND STRENGTHS

For Injection: The Lymphoseek kit contains five vials each containing 250 mcg tilmanocept, and is packaged either with or without five DILUENT for Lymphoseek vials each containing 4.5 mL of sterile buffered saline with phenol. After radiolabeling with technetium Tc 99m and dilution, Lymphoseek contains approximately 92.5 MBq (2.5 mCi) and 250 mcg of technetium Tc 99m tilmanocept in 0.5 mL to 5 mL total volume for injection. (3)

4 CONTRAINDICATIONS

None. (4)

5 WARNINGS AND PRECAUTIONS

Hypersensitivity: Ask patients about prior reactions to drugs, especially dextran or modified forms of dextran. Observe for hypersensitivity signs and symptoms following Lymphoseek injection. Have resuscitation equipment and trained personnel immediately available. (5.1)

6 ADVERSE REACTIONS

The most common adverse reactions (incidence < 1%) are injection site irritation and/or pain. (6.1)

To report SUSPECTED ADVERSE REACTIONS, contact Cardinal Health at 1-800-618-2768 or www.lymphoseek.com or FDA at 1-800-FDA-1088 or www.fda.gov/medwatch

8 USE IN SPECIFIC POPULATIONS

Lactation. To decrease radiation exposure to the breastfed child, advise a lactating woman to pump and discard breast milk after the administration of Lymphoseek for 24 hours. (8.2)

FULL PRESCRIBING INFORMATION

1 INDICATIONS AND USAGE

Lymphoseek is a radioactive diagnostic agent indicated with or without scintigraphic imaging for:

- Lymphatic mapping using a handheld gamma counter to locate lymph nodes draining a primary tumor site in adult and pediatric patients age one month and older with solid tumors for which this procedure is a component of intraoperative management.
- Guiding sentinel lymph node biopsy using a handheld gamma counter in patients with clinically node negative squamous cell carcinoma of the oral cavity, breast cancer or melanoma.

2 DOSAGE AND ADMINISTRATION

2.1 Radiation Safety - Drug Handling

Lymphoseek is a radioactive drug and should be handled with appropriate safety measures to decrease radiation exposure [see Warnings and Precautions (5.2)]. Use waterproof gloves, effective radiation shielding, and appropriate safety measures when preparing and handling Lymphoseek.

Radiopharmaceuticals should be used by or under the control of physicians who are qualified by specific training and experience in the safe use and handling of radionuclides, and whose experience and training have been approved by the appropriate governmental agency authorized to license the use of radionuclides.

2.2 Recommended Dosing

The recommended dose of Lymphoseek is 18.5 MBq (0.5 mCi) as a radioactivity dose and 50 mcg as a mass dose. Administer Lymphoseek at least 15 minutes prior to initiating intraoperative lymphatic mapping and sentinel node biopsy; complete these procedures within 15 hours after Lymphoseek injection.

Route of Administration and Injection Method

The route of administration depends on the tumor location and the planned injection technique and includes: subcutaneous, intradermal, subareolar, or peritumoral injection.

Lymphoseek may be administered to a patient as a single injection or as multiple injections. The recommended total injection volume for each patient (Table 1) is 0.1 mL administered in a single syringe; 0.5 mL administered in a single syringe or in multiple syringes (0.1 mL to 0.25 mL each); or 1 mL administered in multiple syringes (0.2 mL to 0.5 mL each).

The lymphatic system architecture and function may be changed by prior surgery, radiation, edema, inflammation or metastatic disease, and may result in changes to lymph node localization by a radiopharmaceutical or other tracers, including colorimetric agents. Avoid injections into biopsy wound areas that show evidence of edema or inflammation.

In animal studies, locally injected anesthetics have been reported to reduce lymphatic flow. Concomitant administration of local anesthetics with Lymphoseek is not recommended and may impair the lymph nodal mapping.

2.3 Drug Preparation

General Considerations

- Lymphoseek (kit for the preparation of technetium Tc 99m tilmanocept injection) contains five vials, each containing 250 mcg of tilmanocept from which 50 mcg is intended for administration to a patient.
  - The Lymphoseek kit is packaged either with or without five DILUENT for Lymphoseek vials each containing 4.5 mL of sterile buffered saline with phenol.
  - The Lymphoseek kit may also be diluted with pharmacy-available sterile 0.9% sodium chloride injection.
  - A diluent is used to dilute Lymphoseek after the radiolabeling procedure. The amount of diluent used varies, depending on the total injection volume and the number of syringes used for each patient.
- The vial components of the Lymphoseek kit are intended solely for use in the preparation of Lymphoseek. Do not administer the unprepared vial components of the kit directly to a patient.
- Follow aseptic procedures during preparation and administration.

Drug Preparation Instructions

Prior to preparation of Lymphoseek, determine the planned injection technique and the number of injections that will be used for a given patient. For each injection prepare a separate syringe. Based on the planned number of injection syringes and the planned total injection volume per patient, determine (from Table 1 below) the Reconstituted Vial Volume of radiolabeled Lymphoseek.

Table 1. Preparation of Lymphoseek for Administration
Planned Number of Injections for a Patient | Total Injection Volume Per Patient | Reconstituted Vial Volume of Radiolabeled Lymphoseek
1 syringe x 0.1 mL | 0.1 mL | 0.5 mL
5 syringes x 0.1 mL or; 2 syringes x 0.25 mL or; 1 syringe x 0.5 mL | 0.5 mL | 2.5 mL
5 syringes x 0.2 mL or; 4 syringes x 0.25 mL or; 2 syringes x 0.5 mL | 1 mL | 5 mL

Once the Reconstituted Vial Volume is established, use the following steps to prepare radiolabeled Lymphoseek:

Radiolabeling

a. Inspect the Lymphoseek vial for any damage. Do not use if vial integrity appears compromised. Do not vent the Lymphoseek vial prior to or during radiolabeling.

b. Use Sodium Pertechnetate Tc 99m Injection from a technetium Tc 99m generator within 8 hours of its elution.

c. Using a sterile syringe, aseptically draw approximately 92.5 MBq (2.5 mCi) of Sodium Pertechnetate Tc 99m Injection in either about 0.35 mL volume (for 0.5 mL Reconstituted Vial Volume) or about 0.7 mL volume (for 2.5 mL or 5 mL Reconstituted Vial Volume). Assay the syringe for technetium Tc 99m activity in a dose calibrator.

d. Write the radioactivity amount, the Reconstituted Vial Volume, date and time, expiration time and lot number in the space provided on the radioactive product vial label and affix it to the Lymphoseek vial. Place the vial in a radiation shield and sanitize the septum with alcohol wipe.

e. Aseptically add Sodium Pertechnetate Tc 99m Injection to the Lymphoseek vial. Without withdrawing the needle, remove an equal volume of headspace gas. Do not vent.

f. Remove the needle, gently shake the vial to mix the contents, and then let it stand at room temperature for at least 15 minutes.

Reconstitution

g. Aseptically add the supplied DILUENT for Lymphoseek or pharmacy-available sterile 0.9% sodium chloride injection to the radiolabeled product in the Lymphoseek vial to bring the volume to the Reconstituted Vial Volume of 0.5 mL, 2.5 mL, or 5 mL prior to filling the patient dose in syringe(s). To normalize pressure, withdraw an equal volume of headspace gas.

h. Each Lymphoseek vial, once radiolabeled and reconstituted, would contain sufficient amount to provide doses for up to four patients when prepared according to the instructions.

Quality Control of Radiolabeled Solution

i. Assay the reconstituted vial for total radioactivity using a dose calibrator. Write the technetium Tc 99m activity concentration, total volume, assay time and date, expiration time, and lot number on the shield label supplied with the kit. Affix the label to the shield.

j. Determine the radiochemical purity of the radiolabeled product [see Dosage and Administration (2.4)]. Do not use if the radiochemical purity is less than 90%.

k. Withdraw the required volume of the radiolabeled product into the required number of syringes. Assay the syringe(s) in a dose calibrator. Write the radioactivity amount, date and time of assay, volume, and expiration time (this is not to exceed 6 hours from preparation time) on the supplied syringe label and affix it to the syringe(s).

Duration of Use and Storage of Radiolabeled Solution

l. Store the radiolabeled Lymphoseek in radiation shielding at room temperature.

m. Use the radiolabeled Lymphoseek within 6 hours of preparation. Discard the unused radiolabeled Lymphoseek.

2.4 Determination of Radiochemical Purity of Radiolabeled Lymphoseek

Determine radiochemical purity of the reconstituted radiolabeled Lymphoseek by Instant Thin Layer Chromatography (ITLC) using either Whatman Grade 1, 3MM, 31ET Chr or Biodex 150-001 Red Strips (cellulose chromatography paper) using the following method:

a. Mark the chromatographic strip for origin, mid and solvent front lines with a pencil as shown below:
b. Apply a small drop (3 - 10 microliters) of the reconstituted product at the center of the origin line chromatography strip. Let the product spot dry.
c. Place the strip into a chromatography chamber containing 1 mL of acetone as the developing solvent. Allow the solvent to migrate to the solvent front line (5 cm from the bottom of the Whatman strips and 3.5 cm for the Biodex strip). Remove the strip from the chamber, let it dry and cut it in half. Count each half of the strip with a suitable radioactivity counting apparatus (dose calibrator or multichannel analyzer).
d. Calculate the percent radiochemical purity (% RCP) as follows:
  % RCP = Counts (activity) in bottom half x 100
  Counts (activity) in bottom half + Counts (activity) in top half
e. Do not use the reconstituted Lymphoseek if the radiochemical purity is less than 90%.

2.5 Lymphatic Mapping and Sentinel Lymph Node Biopsy Following Injection of Lymphoseek

- Lymphoscintigraphy may be used to assist in planning the lymph node mapping procedures. In clinical studies, preoperative scintigraphic imaging was performed using planar imaging techniques and/or SPECT/CT to establish a map of nodal basins and to facilitate intraoperative identification of lymph nodes. Imaging was performed as early as immediately after injection and up to 21 hours [see Clinical Studies (14)].
- Use a handheld gamma counter to identify nodes that concentrated the injected radioactivity.
- For intraoperative lymphatic mapping, first measure the background radioactivity counts from tissue at least 20 centimeters distal to the injection site. The three sigma threshold (background radioactivity counts plus three times the square root of the mean background count) may be used as an estimate of the threshold for positive localization of Lymphoseek, as exemplified in Table 2.

Table 2. Examples of Three Sigma Threshold Values
Background Counta (cpm) | Threshold Value (cpm)
5 | 12
10 | 20
15 | 27
20 | 34
25 | 40
30 | 47
35 | 53
40 | 59
a Average of three 2-second counts or one 10-second count

- Lymphoseek is intended to supplement palpation, visual inspection, and other procedures important to lymph node mapping and sentinel node biopsy. Intraoperative lymphatic mapping and sentinel node biopsy using gamma detection of Lymphoseek within lymph nodes should be initiated no sooner than 15 minutes following injection. In clinical studies of breast cancer and melanoma, patients also received a concomitant blue dye tracer for comparative detection of lymph nodes. While most lymph nodes were detected with Lymphoseek, some were detected only with the blue dye tracer or only with palpation [see Clinical Studies (14)].

2.6 Radiation Dosimetry

- The radiation doses to organs and tissues of an adult patient weighing 70 kg given 18.5 MBq (0.5 mCi) of Lymphoseek are shown in Table 3. For pediatric patients, effective dose equivalent ranged from 355 microSv to 1,232 microSv.

Table 3. Estimated Absorbed Radiation Dose from 18.5 MBq (0.5 mCi) Lymphoseek in Adult Patients with Breast Cancer and Melanoma
Target Organ | Breast Cancera mGy (rad) | Melanomab mGy (rad)
brain | 0.003 (0.0003) | 0.0927 (0.0093)
breast (injection site) | 1.659 (0.1659) | 0.7903 (0.079)
gall bladder wall | 0.0349 (0.0035) | 0.0712 (0.0071)
lower large intestine wall | 0.0123 (0.0012) | 0.057 (0.0057)
small intestine | 0.0101 (0.001) | 0.0594 (0.0059)
stomach | 0.0184 (0.0018) | 0.0562 (0.0056)
upper large intestine wall | 0.0125 (0.0012) | 0.0582 (0.0058)
kidney | 0.1863 (0.0186) | 0.278 (0.0278)
liver | 0.0324 (0.0032) | 0.0929 (0.0093)
lungs | 0.0374 (0.0037) | 0.0599 (0.006)
muscle | 0.0092 (0.0009) | 0.0451 (0.0045)
ovaries | 0.187 (0.0187) | 0.2991 (0.0299)
red marrow | 0.0127 (0.0013) | 0.0507 (0.0051)
bone | 0.0177 (0.0018) | 0.0878 (0.0088)
spleen | 0.0285 (0.0029) | 0.0598 (0.006)
testes | 0.0501 (0.005) | 0.1043 (0.0104)
thymus | 0.1168 (0.0117) | 0.0577 (0.0058)
thyroid | 0.088 (0.0088) | 0.0464 (0.0046)
urinary bladder | 0.0586 (0.0059) | 0.1401 (0.014)
total body | 0.0195 (0.0019) | 0.0547 (0.0055)
Effective Dose Equivalent; males; females | microSv; 296; 330.2 | microSv; 202.4; 251.1
a Calculated from data of 18 patients with breast cancer who received four peritumoral injections of 4 mcg, 20 mcg, and 100 mcg doses of Lymphoseek.
b Calculated from data of 18 patients with melanoma who received four intradermal injections of 20 mcg, 100 mcg, and 200 mcg doses of Lymphoseek. Due to the differences in injection sites among patients with melanoma, the injection site was assumed to be the breast for the purposes of this calculation, as it represents the nearest anatomical construct for the skin from the anatomical sites appropriately included in the estimates.

3 DOSAGE FORMS AND STRENGTHS

For Injection: Lymphoseek (kit for preparation of technetium Tc 99m tilmanocept injection) is supplied as five vials each containing 250 mcg tilmanocept, and is packaged either with or without five DILUENT for Lymphoseek vials each containing 4.5 mL of sterile buffered saline with phenol. After radiolabeling with technetium Tc 99m, Lymphoseek contains approximately 92.5 MBq (2.5 mCi) and 250 mcg technetium Tc 99m tilmanocept in 0.5 mL to 5 mL total volume.

4 CONTRAINDICATIONS

None.

5 WARNINGS AND PRECAUTIONS

5.1 Hypersensitivity Reactions

Lymphoseek may pose a risk of hypersensitivity reactions due to its chemical similarity to dextran [see Description (11)]. Serious hypersensitivity reactions have been associated with dextran and modified forms of dextran (such as iron dextran drugs).

Before administering Lymphoseek, ask patients about prior hypersensitivity reactions to drugs, especially to dextran and modified forms of dextran. Have resuscitation equipment and trained personnel immediately available at the time of Lymphoseek administration.

5.2 Radiation Risks

Any radiation-emitting product may increase the risk for cancer, especially in pediatric patients. Adhere to the dose recommendations and ensure safe handling to decrease the risk for excessive radiation exposure to either patients or health care workers.

6 ADVERSE REACTIONS

6.1 Clinical Trials Experience

Because clinical trials are conducted under widely varying conditions, adverse reaction rates observed in the clinical trials of a drug cannot be directly compared to rates in the clinical trials of another drug and may not reflect the rates observed in practice.

In open label, single arm clinical trials, 553 adult patients with either breast cancer, melanoma, or squamous cell carcinoma of the oral cavity, skin, and lip received Lymphoseek. No patients experienced serious adverse reactions. Injection site irritation (4 patients; 0.7%) and pain (1 patient; 0.2%) were reported.

8 USE IN SPECIFIC POPULATIONS

8.1 Pregnancy

Risk Summary

There are no available data on Lymphoseek use in pregnant women. Additionally, animal reproduction studies have not been conducted with technetium Tc 99m tilmanocept. However, all radiopharmaceuticals, including Lymphoseek, have a potential to cause fetal harm depending on the fetal stage of development and the magnitude of the radiation dose. If considering Lymphoseek administration to a pregnant woman, inform the patient about the potential for adverse pregnancy outcomes based on the radiation dose from the drug and the gestational timing of exposure.

The estimated background risk of major birth defects and miscarriage for the indicated population is unknown. All pregnancies have a background risk of birth defect, loss, or other adverse outcomes. In the U.S. general population, the estimated background risks of major birth defects and miscarriage in clinically recognized pregnancies are 2 to 4% and 15 to 20%, respectively, regardless of drug exposure.

8.2 Lactation

Risk Summary

No data are available regarding the presence of technetium Tc 99m tilmanocept in human milk, the effects of the drug on the breastfed child, or the effects of the drug on milk production. Exposure of Lymphoseek to a breastfed child can be decreased by temporary discontinuation of breastfeeding [see Clinical Considerations]. The developmental and health benefits of breastfeeding should be considered along with the mother’s clinical need for Lymphoseek and any potential adverse effects on the breastfed child from Lymphoseek or from the underlying maternal condition.

Clinical Considerations

To decrease radiation exposure to the breastfed child, advise a lactating woman to pump and discard breast milk after the administration of Lymphoseek for 24 hours.

8.4 Pediatric Use

The safety and effectiveness of Lymphoseek have been established in pediatric patients 1 month of age and older. Use of Lymphoseek for this population is supported by evidence from adequate and well-controlled studies in adults with additional safety and diagnostic data from an open-label, single-arm trial in 23 pediatric patients with either melanoma (5), rhabdomyosarcoma (4), or other solid tumors (14) who received Lymphoseek (18.5 MBq and 50 mcg) and underwent intraoperative lymphatic mapping, with or without additional use of preoperative scintigraphic imaging and/or blue dye [see Clinical Studies (14.1)]. Review of the clinical data, including evaluation of the frequency of adverse reactions and localization of lymph nodes, has not identified differences in safety or efficacy between pediatric patients and older patients.

8.5 Geriatric Use

Of the 553 adult patients enrolled in clinical studies of breast cancer, melanoma, and squamous cell carcinoma (SCC) of oral cavity, skin, and lip, 179 (32%) were aged 65 or older. Review of the clinical data, including evaluation of the frequency of adverse reactions, has not identified differences in safety or efficacy between elderly patients (65 to 90 years of age) and younger adult patients (18 to 65 years of age).

11 DESCRIPTION

Chemical Characteristics

The active ingredient in Lymphoseek, a radioactive diagnostic agent, is technetium Tc 99m tilmanocept. Technetium Tc 99m binds to the diethylenetriaminepentaacetic acid (DTPA) moieties of the tilmanocept molecule.

- Chemically, technetium Tc 99m tilmanocept consists of technetium Tc 99m, dextran 3-[(2-aminoethyl)thio]propyl 17-carboxy-10,13,16-tris(carboxymethyl)-8-oxo-4-thia-7,10,13,16-tetraazaheptadec-1-yl 3-[[2-[[1-imino-2-(D-mannopyranosylthio)ethyl]amino]ethyl]thio]propyl ether complexes.
- The molecular formula of technetium Tc 99m tilmanocept is [C6H10O5]n.(C19H28N4O9S99mTc)b.(C13H24N2O5S2)c.(C5H11NS)a. It contains 3-8 conjugated DTPA (diethylenetriaminepentaacetic acid) molecules (b); 12-20 conjugated mannose molecules (c) with 0-17 amine side chains (a) remaining free.
- The calculated average molecular weight of tilmanocept ranges from 15,281 to 23,454 g/mol.
- Technetium Tc 99m tilmanocept has the following structural formula:

Lymphoseek is supplied as a kit which contains five vials, 250 mcg tilmanocept per vial. Each Lymphoseek vial contains the non-radioactive ingredients needed to produce technetium Tc 99m tilmanocept. The vial contains a sterile, non-pyrogenic, white to off-white lyophilized powder (under nitrogen) that consists of a mixture of 250 mcg tilmanocept, 20 mg trehalose dihydrate, 0.5 mg glycine, 0.5 mg sodium ascorbate, and 0.075 mg stannous chloride dihydrate. Sodium hydroxide and hydrochloric acid may be used to adjust the pH prior to lyophilization.

The DILUENT for Lymphoseek contains 4.5 mL sterile buffered saline consisting of 0.04% (w/v) potassium phosphate, 0.11% (w/v) sodium phosphate (heptahydrate), 0.5% (w/v) sodium chloride, and 0.4% (w/v) phenol.

Physical Characteristics

Technetium Tc 99m decays by isomeric transition with a physical half-life of approximately 6 hours. The principal photon that is useful for detection and imaging studies is listed in Table 4.

Table 4. Principal Radiation Emission Data
Radiation | Mean % Disintegration | Mean Energy (keV)
Gamma-2 | 89.1 | 140.5
From: Kocher, D.C. Radioactive decay data tables. DOE/TIC-11026, 108 (1981).

External Radiation

The linear mass energy absorption attenuation coefficient for Tc 99m is 18.9 cm^-1. The first half-value layer is 0.037 cm of lead (Pb). The use of a 0.25 cm thick standard radiation lead shield will attenuate the radiation emitted by millicurie amounts of technetium Tc 99m by a factor of about 100. A range of values for the relative attenuation of the radiation of technetium Tc 99m that results with various thicknesses of lead shielding are displayed in Table 5.

Table 5. Radiation Attenuation by Lead Shielding
Shield Thickness, cm of lead (Pb) | Coefficient of Attenuation
0.037 | 0.5
0.12 | 10^-1
0.24 | 10^-2
0.36 | 10^-3
0.49 | 10^-4

To correct for physical decay of the radionuclide, the fractions that remain at selected intervals after the time of calibration are shown in Table 6.

Table 6. Physical Decay Chart; Tc 99m, Half-Life of approximately 6 Hours
Hours | Fraction Remaining
0 | 1
1 | 0.891
3 | 0.708
6 | 0.501
12 | 0.251
15 | 0.178

12 CLINICAL PHARMACOLOGY

12.1 Mechanism of Action

Lymphoseek (technetium Tc 99m tilmanocept) is a radioactive diagnostic agent. It accumulates in lymphatic tissue and selectively binds to mannose binding receptors (CD206) located on the surface of macrophages and dendritic cells. Technetium Tc 99m tilmanocept is a macromolecule consisting of multiple units of diethylenetriaminepentaacetic acid (DTPA) and mannose, each covalently attached to a 10 kDa dextran backbone. The mannose acts as a ligand for the receptor, and the DTPA serves as a chelating agent for labeling with technetium Tc 99m.

12.2 Pharmacodynamics

In in vitro studies, technetium Tc 99m tilmanocept exhibited binding to human mannose binding receptors with a primary binding site affinity of Kd = 2.76 x 10^-11 M.

In clinical studies, technetium Tc 99m tilmanocept has been detectable in lymph nodes within 10 minutes and up to 30 hours after injection.

12.3 Pharmacokinetics

In dose-ranging clinical studies, injection site clearance rates were similar across all Lymphoseek doses (4 to 200 mcg) with a mean elimination rate constant in the range of 0.222 to 0.396/hr, resulting in a drug half-life at the injection site of 1.8 to 3.1 hours.

The amount of the accumulated radioactive dose in the liver, kidney, and bladder reached a maximum 1 hour post administration of Lymphoseek and was approximately 1% to 2% of the injected dose in each tissue.

13 NONCLINICAL TOXICOLOGY

13.1 Carcinogenesis, Mutagenesis, Impairment of Fertility

Studies to assess the carcinogenicity potential of tilmanocept have not been conducted. Tilmanocept was not mutagenic in vitro in the Ames bacterial mutation assay and in the in vitro mouse lymphoma test, and was negative in the in vivo micronucleus test in mice.

Studies on reproductive fertility have not been conducted.

14 CLINICAL STUDIES

14.1 Overview of Clinical Studies

The efficacy and safety of Lymphoseek were assessed in three open-label, multicenter, single arm trials of adult patients with melanoma, breast cancer, or squamous cell carcinoma (SCC) of the oral cavity, skin, and lip (Studies 1, 2, and 3) and one open-label, multicenter, single arm trial of pediatric patients with melanoma, rhabdomyosarcoma, or other solid tumor (Study 4). Prior to the lymph node mapping and sentinel lymph node biopsy procedures, patients had no known regional nodal or metastatic disease by standard clinical staging criteria.

- In Studies 1 and 2, Lymphoseek was evaluated in adult patients with breast cancer and melanoma. Diagnostic efficacy for lymphatic mapping was determined by the number of histology-confirmed lymph nodes detected by Lymphoseek and/or the blue dye comparator. Lymphoseek was injected into patients at least 15 minutes prior to initiating lymphatic mapping procedures, and preoperative scintigraphic imaging was performed in 91% of patients. Separately, blue dye was injected shortly prior to initiation of the surgery. Lymphatic mapping was performed intraoperatively using a handheld gamma detection probe followed by excision of lymph nodes identified by Lymphoseek, blue dye, or the surgeon’s visual and palpation examination. The resected lymph nodes were evaluated by histopathology. Lymphoseek localization rate in pathology-positive lymph nodes was also determined.
  - In Study 1, of 179 patients who received Lymphoseek, 94 (53%) had known or suspected breast cancer and 85 (47%) had known or suspected melanoma. The median age was 59 years (range 20 to 90 years) and most (72%) were female.
  - In Study 2, of 153 patients who received Lymphoseek, 77 (50%) had known or suspected breast cancer and 76 (50%) had known or suspected melanoma. The median age was 61 years (range 26 to 88 years) and most (68%) were female.
- In Study 3, Lymphoseek was evaluated in adult patients primarily with SCC of the oral cavity (T1-T4a, N0, M0). Diagnostic efficacy was determined by the patient level false negative rate of sentinel lymph node detection by Lymphoseek as confirmed by pathologic assessment of all lymph nodes removed during planned elective neck dissection (END). Lymphoseek was administered at least 15 minutes prior to the scheduled surgery and preoperative scintigraphic imaging was performed in all patients. Lymphatic mapping was performed intraoperatively using a handheld gamma counter followed by excision of sentinel lymph nodes identified by Lymphoseek. Additional lymph nodes were removed during the END based upon tumor location and surgical practice. All resected lymph nodes (sentinel and non-sentinel) were evaluated for histopathology at the local site. Lymphoseek-identified nodes determined negative for cancer were further evaluated by a central pathology laboratory using additional step sectioning and cytokeratin staining.
  - Of the 85 patients who received Lymphoseek, 79 (93%) had intraoral SCC and 6 (7%) had cutaneous SCC. The median age was 59 years (range 23 to 87 years) and most (75%) were male.
- In Study 4, Lymphoseek was evaluated in pediatric patients with melanoma, rhabdomyosarcoma, or other solid tumor. Safety and diagnostic efficacy for lymphatic mapping were determined. Lymphoseek was injected into patients at least 15 minutes prior to initiating lymphatic mapping procedures, and preoperative scintigraphic imaging was performed in 91% of patients. Blue dye was injected prior to initiation of the surgery in 21 patients. Lymphatic mapping was performed intraoperatively using a handheld gamma detection probe followed by excision of lymph nodes identified by Lymphoseek, blue dye (when used adjunctively), or the surgeon’s visual and palpation examination. The resected lymph nodes were evaluated by histopathology. Lymphoseek localization rate in pathology-positive lymph nodes was also determined.
  - Of the 23 patients who received Lymphoseek, 5 (22%) had melanoma, 4 (17%) had rhabdomyosarcoma, 12 (52%) had non-rhabdomyosarcoma soft tissue sarcomas, and 2 (9%) had atypical Spitz nevi. The mean age was 11.6 years (range 1.7 to 17 years) and most (65%) were female.

14.2 Lymphoscintigraphy

An analysis of the four studies was performed to evaluate the agreement in location of lymph nodes identified by scintigraphic imaging and the handheld gamma counter. At least one scintigraphic “hot spot” was identified in 95% of patients imaged; the percentages were similar across tumor types and age groups. Overall in the adult patients, there was 84% agreement on a nodal level (when considering all missing observations as disagreement, as worst case scenario) between the location of preoperative scintigraphic imaging hot spots and the intraoperative lymph node findings (Table 7). Missing observations took the following form: 43 hot spots without corresponding hot nodes and 31 hot nodes without corresponding hot spots.

Table 7. Location Agreement between Scintigraphic Imaging and Gamma Counter Findings in Adult Patients
 | Melanoma | Breast Cancer | Head and Neck Cancer | Overall Results
Agreement of Hot Spot and Hot Node Location* | 182/206;; 88%; (83%, 93%)** | 116/147;; 79%; (70%, 88%)** | 95/115;; 83%; (76%, 90%)** | 393/468;; 84%; (81%, 87%)**
* Denominator equals total number of hot spots and/or hot nodes. Numerator equals the numbers where hot spots and hot nodes agreed in location.
** 95% Confidence Intervals.

14.3 Lymphatic Mapping

In Studies 1 and 2 in adult melanoma and breast cancer, efficacy analyses were based upon comparisons of the number and proportion of resected lymph nodes that contained a lymph node tracer (Lymphoseek and/or blue dye) or neither tracer. Evaluable lymph nodes were resected from 176 Study 1 patients and 152 Study 2 patients who received Lymphoseek at the dose of 0.5 to 2 mCi in 50 mcg administered 15 minutes to 30 hours prior to surgery. Table 8 shows the distribution of resected lymph nodes by the presence or absence of a tracer. Most of the resected lymph nodes were identified by either Lymphoseek (LS) or blue dye (BD) or both. Significantly more resected lymph nodes were identified by Lymphoseek in comparison to blue dye.

Table 8. Resected Lymph Nodes and Content of Lymphoseek (LS) and/or Blue Dye (BD) from Studies in Adult Breast Cancer and Melanoma
Study | Tumor | Nodes n | BD Present % (95% CI) | LS Present % (95% CI) | Only BD Present % (95% CI) | Only LS Present % (95% CI) | Neither BD nor LS Present % (95% CI)
One | Melanoma | 187 | 65% (57% , 72%) | 93% (88% , 96%) | 2% (0 , 5%) | 29% (23% , 37%) | 6% (3% , 10%)
One | Breast Cancer | 192 | 70% (63% , 77%) | 89% (83% , 93%) | 7% (4% , 12%) | 26% (20% , 32%) | 4% (2% , 8%)
Two | Melanoma | 198 | 59% (51% , 66%) | 99% (97% , 100%) | 0 (0 , 2%) | 41% (34% , 48%) | 1% (0 , 3%)
 | Breast Cancer | 181 | 62% (55% , 70%) | 100% (98% , 100%) | 0 (0 , 2%) | 38% (30% , 45%) | 0 (0 , 2%)
The percentages may not add to 100% due to rounding.
95% Confidence Intervals (CI) are based on Exact Binomial and represent the spread in the individual estimates.

In Studies 1 and 2 lymphatic mapping was performed in 328 adult patients with melanoma or breast cancer. The overall rate of lymph node detection by Lymphoseek at the patient level was 97% (319/328). The average number of lymph nodes detected by Lymphoseek was approximately 2 per patient.

In Study 3 lymphatic mapping was performed in 83 adult patients with SCC of the oral cavity. The rate of lymph node detection by Lymphoseek at the patient level was 98% (81/83) with a 95% confidence interval of 92% to 100%. The average number of lymph nodes identified was 4 per patient.

In Study 4 lymphatic mapping was performed in 23 pediatric patients with melanoma, rhabdomyosarcoma, and other solid tumors. The overall rate of lymph node detection by Lymphoseek at the patient level was 96% (22/23) when the detection rate is defined as at least one lymph node in a patient can be detected. The average number of lymph nodes detected by Lymphoseek was approximately 3 per patient. Of the 79 nodes in 21 patients who also received blue dye, all of 47 nodes identified by blue dye were also identified by Lymphoseek; a total of 74 nodes were identified by Lymphoseek.

14.4 Guiding Sentinel Lymph Node Biopsy

In Study 3 in patients with SCC of the oral cavity (n=79), skin (n=5), and lip (n=1), pathology findings for Lymphoseek-identified nodes (sentinel lymph nodes) were compared to the pathology findings of all other lymph nodes removed during the scheduled elective node dissection to determine the false negative rate of Lymphoseek. Thirty-nine patients were determined to have pathology-positive regional lymph nodes. In these patients, the Lymphoseek false negative rate for detecting patients with cancer-positive nodes was 2.6% (95% CI: 0.06% to 13.5%). In this study the pathology-positive nodes were all found in patients with SCC of the oral cavity.

Supportive analyses were conducted in Studies 1 and 2 in patients with breast cancer or melanoma, and Study 4 in pediatric patients. The presence or absence of Lymphoseek in nodes resected from patients determined by pathology staging to have lymphatic spread of cancer (n=66) was evaluated. The overall patient level rate for identifying at least one cancer-positive node in these pathology-positive patients (both cancers combined) was 97%. Lymphoseek identified 27 out of 29 node positive adult patients with breast cancer, all of the 35 node positive adult patients with melanoma, and both of the 2 node positive pediatric patients (1 melanoma and 1 rhabdomyosarcoma).

16 HOW SUPPLIED/STORAGE AND HANDLING

16.1 How Supplied

The Lymphoseek (kit for the preparation of technetium Tc 99m tilmanocept injection) (NDC 65857-425-05) includes:

- Five Lymphoseek kit vials (250 mcg tilmanocept per vial) NDC 65857-400-01
- Prescribing information
- Five labels for shields
- Twenty-five labels for product vials and individual syringes

The Lymphoseek (kit for the preparation of technetium Tc 99m tilmanocept injection) (NDC 65857-450-05) includes:

- Five Lymphoseek kit vials (250 mcg tilmanocept per vial) NDC 65857-400-01
- Five vials of DILUENT for Lymphoseek (NDC 65857-401-45)
- Prescribing information
- Five labels for shields
- Twenty-five labels for product vials and individual syringes

16.2 Storage and Handling

Storage

Store Lymphoseek (kit for the preparation of technetium Tc 99m tilmanocept injection) in the original packaging at 20° to 25°C (68° to 77°F); excursions permitted to 15° to 30°C (59° to 86°F) [see USP Controlled Room Temperature].

Store radiolabeled Lymphoseek in radiation shielding at room temperature.

Use radiolabeled Lymphoseek within 6 hours of preparation. Discard unused portion.

Handling

This Lymphoseek (kit for the preparation of technetium Tc 99m tilmanocept injection) is approved for distribution to persons licensed by the U.S. Nuclear Regulatory Commission to use by product material identified in 10 CFR 35.200 or under an equivalent license issued by an Agreement State.

17 PATIENT COUNSELING INFORMATION

- Advise patients to seek medical attention for reactions following injection of Lymphoseek such as difficulty breathing, skin rash, or other allergy manifestations.
- Inform nursing women to pump and discard breast milk for at least 24 hours following administration of Lymphoseek injection [see Use in Specific Populations (8.2)].

Distributed by:

Cardinal Health 414, LLC
Dublin, OH 43017

Lymphoseek is a registered trademark of Cardinal Health 414, LLC.

Patent: www.lymphoseek.com/patent-information

PRINCIPAL DISPLAY PANEL - Carton

Carton

Principal Display Panel

NDC 65857-450-05

Lymphoseek®
(kit for the preparation of
technetium Tc 99m tilmanocept
injection)

250 mcg Tilmanocept per Vial

Multiple-Dose Kit

Contents:

- Five Lymphoseek kit vials (250 mcg tilmanocept per vial) NDC 65857-400-01
- Five vials of DILUENT for Lymphoseek NDC 65857-401-45
- Prescribing information
- Five Radioassay information shield labels
- Twenty-five labels for product vials and individual syringes

Store kit in the original packaging at 20° to 25°C (68° to 77°F); excursions
permitted to 15° to 30°C (59° to 86°F) [See USP Controlled Room Temperature].

See Prescribing Information for preparation and administration instructions.

For subcutaneous, intradermal, subareolar, or peritumoral use.

Use within 6 hours after reconstitution. Discard unused portion.

Pat: www.lymphoseek.com/patent-information

Distributed by Cardinal Health 414, LLC
Dublin, OH 43017

Rx Only

Back Panel

Lymphoseek®
(kit for the preparation of
technetium Tc 99m tilmanocept
injection)

250 mcg Tilmanocept per Vial

Each sterile, non-pyrogenic, lyophilized powder vial contains:

Tilmanocept 250 mcg
Trehalose, Dihydrate 20 mg
Glycine 0.5 mg
Sodium Ascorbate 0.5 mg
Stannous Chloride, Dihydrate 0.075 mg
Sodium hydroxide and hydrochloric acid may be used to adjust the pH.
The Lymphoseek kit vials are sealed under nitrogen at the time of manufacture,
and contain no preservatives.

DILUENT for Lymphoseek contains:
Each vial contains 4.5 mL sterile, non-pyrogenic, aqueous solution of:
Potassium Phosphate 0.04% w/v
Sodium Phosphate-7H2O 0.11% w/v
Sodium Chloride 0.50% w/v
Phenol 0.40% w/v

Rx Only

For Customer Service call: 1-800-476-5270
Website: www.lymphoseek.com

CardinalHealth™

7-C001685E

Lot:

Exp:

Left Side Panel

Lymphoseek® (kit for the preparation of technetium Tc 99m tilmanocept injection)

WARNING: Radiopharmaceuticals should be used by persons who are qualified by specific training in the safe
use and handling of radionuclides and whose experience and training have been approved by the appropriate
governmental agency authorized to license the use of nuclides.

Right Side Panel

Storage Conditions:

Store kit in the original packaging at 20° to 25°C (68° to 77°F); excursions permitted
to 15° to 30°C (59° to 86°F) [See USP Controlled Room Temperature].

PRINCIPAL DISPLAY PANEL - DILUENT

Diluent Label

NDC 65857-401-45

DILUENT for Lymphoseek

For diluting radiolabeled Lymphoseek only

Not for direct administration

See package insert for preparation and
administration instructions.

Single Dose Vial - Discard unused portion.

Rx Only 23001105-C04

Contents: 4.5 mL non-pyrogenic, aqueous
solution of 0.04% w/v Potassium Phosphate,
0.11% w/v Sodium Phosphate (Heptahydrate),
0.50% w/v Sodium Chloride and 0.40% w/v
Phenol.

Store in the original packaging at 20° to 25°C
(68° to 77°F), excursions permitted to 15° to
30°C (59° to 86°F) [See USP Controlled Room
Temperature].

Distributed by:
Cardinal Health 414, LLC
Dublin, OH 43017